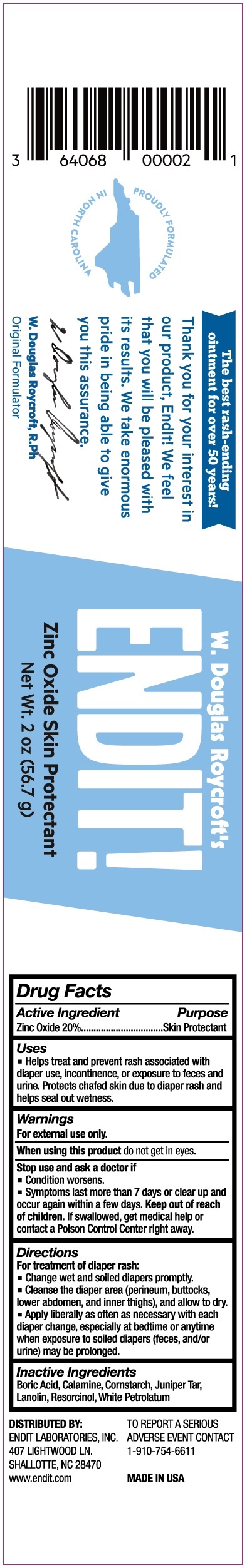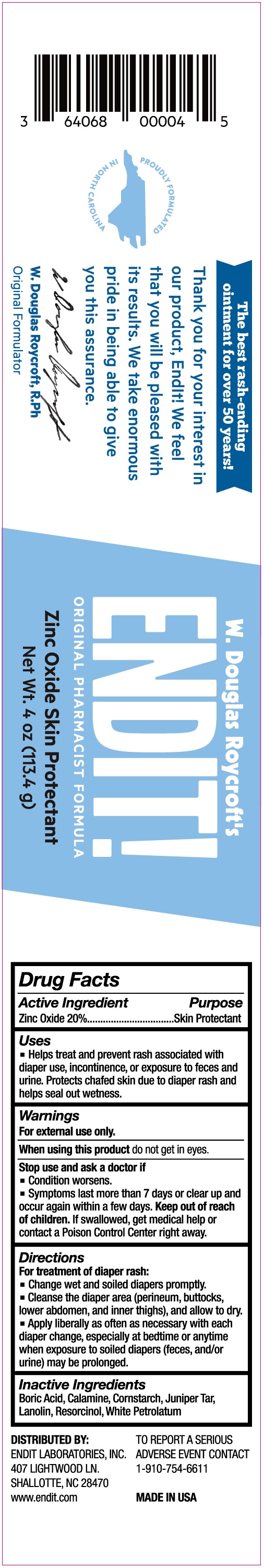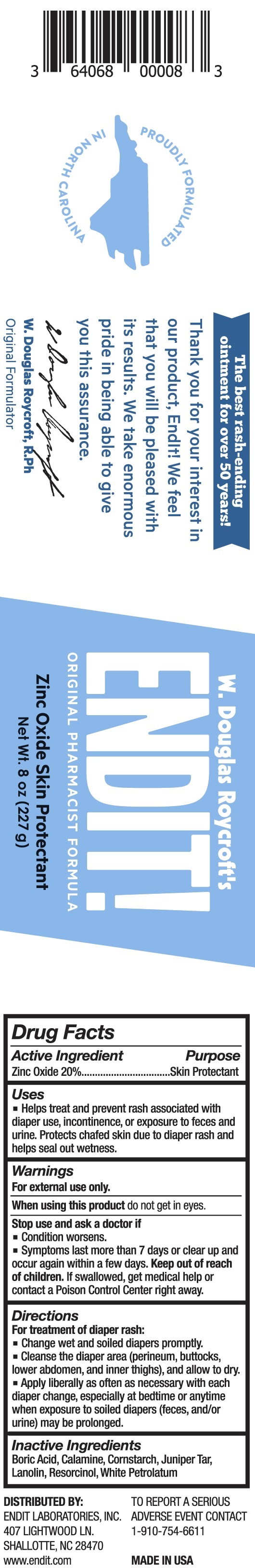 DRUG LABEL: Endit zinc oxide skin protection
NDC: 64068-500 | Form: OINTMENT
Manufacturer: EndIt Laboratories, Inc.
Category: otc | Type: HUMAN OTC DRUG LABEL
Date: 20231215

ACTIVE INGREDIENTS: ZINC OXIDE 200 mg/1 g
INACTIVE INGREDIENTS: BORIC ACID; STARCH, CORN; JUNIPER TAR; LANOLIN; RESORCINOL; WHITE PETROLATUM

Endit zinc oxide skin protection

Active Ingredient

Zinc Oxide 20%

Purpose

Skin Protectant

Uses

- Helps treat and prevent rash associated with diaper use, incontinence, or exposure to feces and urin, Protects chafed skin due to diaper rash and helps seal out wetness.

Warnings

For external use only.

When using this product

do not get in eyes.

Stop use and ask a doctor if

- Condition worsens.
- Symptoms last more than 7 days or clear up and occur again within a few days.

Keep out of reach of children.

If swallowed, get medical help or contact a Poison Control Center right away.

Directions

For treatment of diaper rash:

- Change wet and soiled diapers promptly.
- Cleanse the diaper area (perineum, buttocks, lower abdomen, and inner thighs), and allow to dry.
- Apply liberally as often as necessary with each diaper change, especially at bedtime or anytime when exposure to soiled diapers (feces, and/or urine) may be prolonged.

Inactive Ingredients

Boric Acid, Calamine, Cornstarch, Juniper Tar, Lanolin, Resorcinol, White Petrolatum